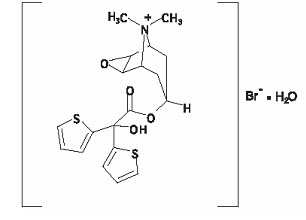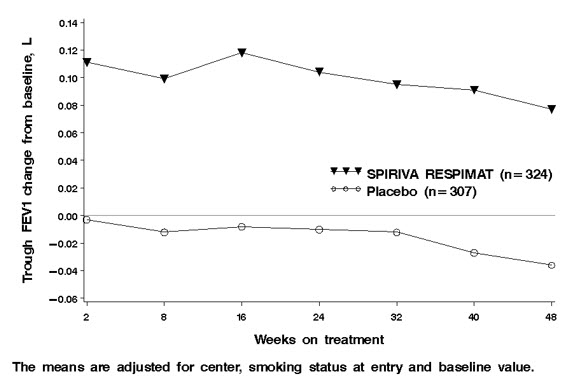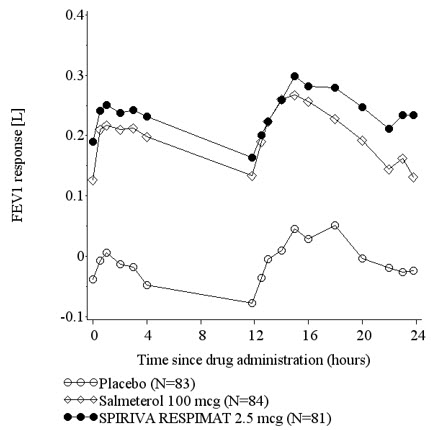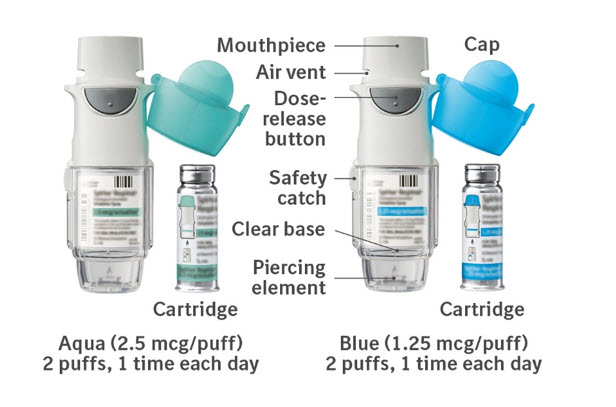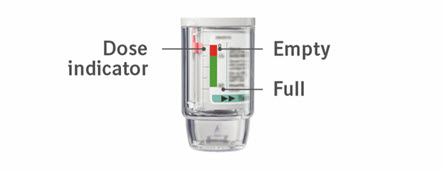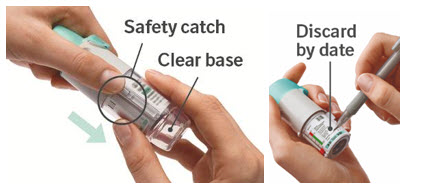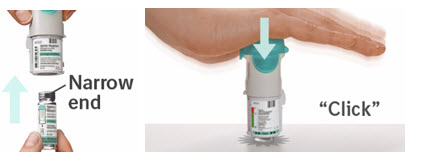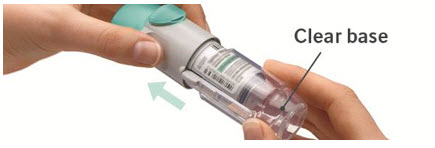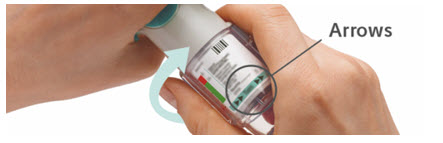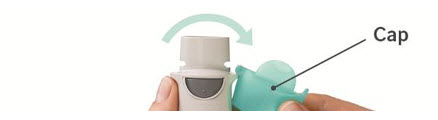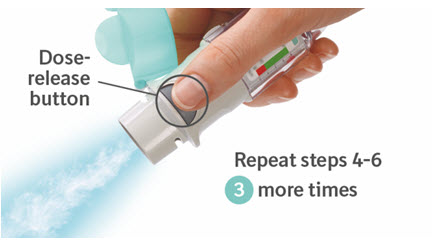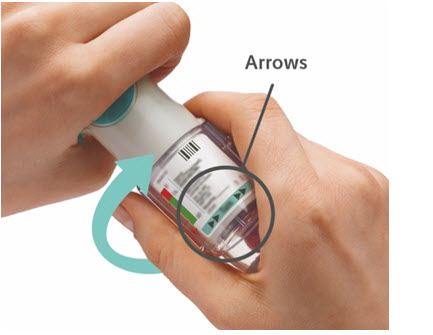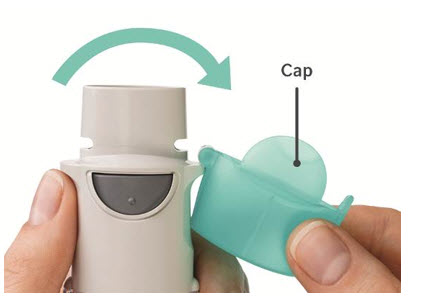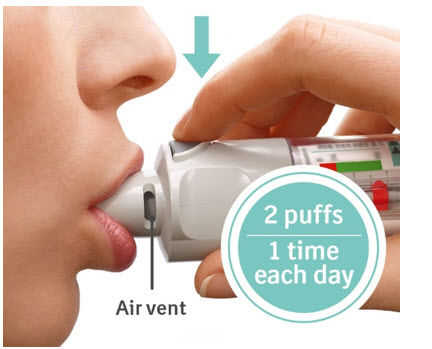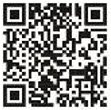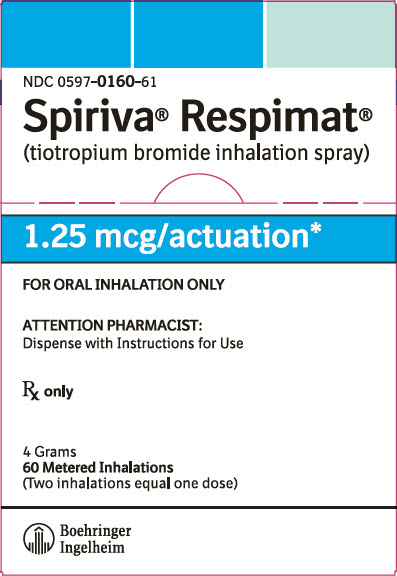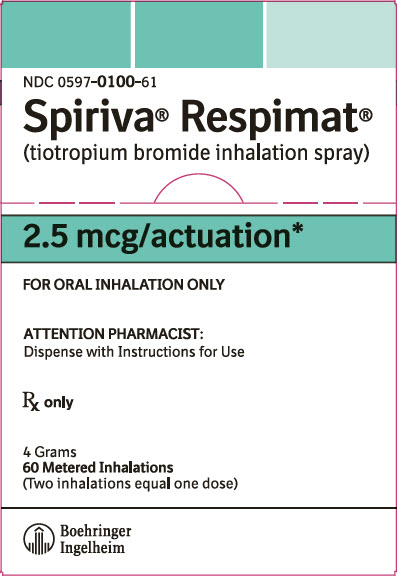 DRUG LABEL: Spiriva Respimat
NDC: 0597-0160 | Form: SPRAY, METERED
Manufacturer: Boehringer Ingelheim Pharmaceuticals, Inc.
Category: prescription | Type: HUMAN PRESCRIPTION DRUG LABEL
Date: 20251125

ACTIVE INGREDIENTS: TIOTROPIUM BROMIDE ANHYDROUS 1.562 ug/1 1

HIGHLIGHTS OF PRESCRIBING INFORMATION

These highlights do not include all the information needed to use SPIRIVA RESPIMAT safely and effectively. See full prescribing information for SPIRIVA RESPIMAT.
SPIRIVA® RESPIMAT® (tiotropium bromide inhalation spray), for oral inhalation use
Initial U.S. Approval: 2004

1 INDICATIONS AND USAGE

SPIRIVA RESPIMAT is an anticholinergic indicated for:

- The long-term, once-daily, maintenance treatment of bronchospasm associated with chronic obstructive pulmonary disease (COPD), and for reducing COPD exacerbations (1.1)
- The long-term, once-daily, maintenance treatment of asthma in patients 6 years of age and older (1.2)

Limitation of Use:

- Not indicated for relief of acute bronchospasm (1.1, 1.2, 5.1)

2 DOSAGE AND ADMINISTRATION

For oral inhalation only.

To receive the full dose of medication, SPIRIVA RESPIMAT must be administered as two inhalations once-daily.

- Treatment of COPD: 2 inhalations of SPIRIVA RESPIMAT 2.5 mcg once-daily. (2)
- Treatment of asthma patients 6 years and older: 2 inhalations of SPIRIVA RESPIMAT 1.25 mcg once-daily. (2)

3 DOSAGE FORMS AND STRENGTHS

- Inhalation spray: 1.25 mcg or 2.5 mcg tiotropium (equivalent to 1.562 mcg or 3.124 mcg, respectively, of tiotropium bromide monohydrate) per actuation with the SPIRIVA RESPIMAT inhaler. Two actuations equal one dose (2.5 mcg or 5 mcg). (3)

4 CONTRAINDICATIONS

Hypersensitivity to tiotropium, ipratropium, or any component of this product. (4)

5 WARNINGS AND PRECAUTIONS

- Not for acute use, i.e., not a rescue medication. (5.1)
- Immediate hypersensitivity reactions: Discontinue SPIRIVA RESPIMAT at once and consider alternatives if immediate hypersensitivity reactions, including angioedema, urticaria, rash, bronchospasm, or anaphylaxis, occur. (5.2)
- Paradoxical bronchospasm: Discontinue SPIRIVA RESPIMAT and consider other treatments if paradoxical bronchospasm occurs. (5.3)
- Worsening of narrow-angle glaucoma may occur. Use with caution in patients with narrow-angle glaucoma and instruct patients to consult a physician immediately if this occurs. (5.4)
- Worsening of urinary retention may occur. Use with caution in patients with prostatic hyperplasia or bladder-neck obstruction and instruct patient to consult a physician immediately if this occurs. (5.5)

6 ADVERSE REACTIONS

The most common adverse reactions in:

- COPD: (>3% incidence in the placebo-controlled trials with treatment durations of between 4 and 48 weeks) were pharyngitis, cough, dry mouth, and sinusitis. (6.1).
- Asthma: (>2% incidence in the placebo-controlled trials with treatment durations of between 12 and 52 weeks) were pharyngitis, headache, bronchitis, and sinusitis in adults. (6.2).

To report SUSPECTED ADVERSE REACTIONS, contact Boehringer Ingelheim Pharmaceuticals, Inc. at 1-800-542-6257 or FDA at 1-800-FDA-1088 or www.fda.gov/medwatch.

7 DRUG INTERACTIONS

Anticholinergics: May interact additively with concomitantly used anticholinergic medications. Avoid administration of SPIRIVA RESPIMAT with other anticholinergic-containing drugs. (7.2)

8 USE IN SPECIFIC POPULATIONS

Patients with moderate to severe renal impairment should be monitored closely for potential anticholinergic side effects. (2, 8.6)

FULL PRESCRIBING INFORMATION

1 INDICATIONS AND USAGE

1.1 Maintenance Treatment of Chronic Obstructive Pulmonary Disease

SPIRIVA RESPIMAT (tiotropium bromide) is indicated for the long-term, once-daily, maintenance treatment of bronchospasm associated with chronic obstructive pulmonary disease (COPD), including chronic bronchitis and emphysema. SPIRIVA RESPIMAT is indicated to reduce exacerbations in COPD patients.

Important Limitation of Use:

SPIRIVA RESPIMAT is NOT indicated for the relief of acute bronchospasm.

1.2 Maintenance Treatment of Asthma

SPIRIVA RESPIMAT is a bronchodilator indicated for the long-term, once-daily, maintenance treatment of asthma in patients 6 years of age and older.

Important Limitation of Use:

SPIRIVA RESPIMAT is NOT indicated for the relief of acute bronchospasm.

2 DOSAGE AND ADMINISTRATION

To receive the full dosage of medication, SPIRIVA RESPIMAT must be administered as two inhalations once-daily. Do not take more than one dose (2 inhalations) in 24 hours.

Prior to first use, the SPIRIVA RESPIMAT cartridge is inserted into the SPIRIVA RESPIMAT inhaler and the unit is primed. When using the unit for the first time, patients are to actuate the inhaler toward the ground until an aerosol cloud is visible and then repeat the process three more times. The unit is then considered primed and ready for use. If not used for more than 3 days, patients are to actuate the inhaler once to prepare the inhaler for use. If not used for more than 21 days, patients are to actuate the inhaler until an aerosol cloud is visible and then repeat the process three more times to prepare the inhaler for use [see Patient Counseling Information (17)].

2.1 Chronic Obstructive Pulmonary Disease

The recommended dosage for patients with COPD is 2 inhalations of SPIRIVA RESPIMAT 2.5 mcg per actuation once-daily; total dose equals 5 mcg of SPIRIVA RESPIMAT.

2.2 Asthma

The recommended dosage for patients with asthma is 2 inhalations of SPIRIVA RESPIMAT 1.25 mcg per actuation once-daily; total dose equals 2.5 mcg of SPIRIVA RESPIMAT. In the treatment of asthma, the maximum benefits in lung function may take up to 4 to 8 weeks of dosing [see Patient Counseling Information (17)].

2.3 Special Populations

No dosage adjustment is required for geriatric, hepatically-impaired, or renally-impaired patients. However, patients with moderate to severe renal impairment given SPIRIVA RESPIMAT should be monitored closely for anticholinergic effects [see Warnings and Precautions (5.6), Use in Specific Populations (8.5, 8.6, 8.7), and Clinical Pharmacology (12.3)].

3 DOSAGE FORMS AND STRENGTHS

SPIRIVA RESPIMAT consists of a SPIRIVA RESPIMAT inhaler and an aluminum cylinder (SPIRIVA RESPIMAT cartridge) containing tiotropium bromide (as the monohydrate). The SPIRIVA RESPIMAT cartridge is only intended for use with the SPIRIVA RESPIMAT inhaler.

SPIRIVA RESPIMAT is available in two dosage strengths. Each actuation from the SPIRIVA RESPIMAT inhaler delivers 1.25 mcg or 2.5 mcg of tiotropium (equivalent to 1.562 mcg or 3.124 mcg, respectively, of tiotropium bromide monohydrate) from the mouthpiece. Two actuations equal one dose (2.5 mcg or 5 mcg).

4 CONTRAINDICATIONS

SPIRIVA RESPIMAT is contraindicated in patients with a hypersensitivity to tiotropium, ipratropium, or any component of this product [see Warnings and Precautions (5.2)]. In clinical trials with SPIRIVA RESPIMAT, immediate hypersensitivity reactions, including angioedema (including swelling of the lips, tongue, or throat), itching, or rash have been reported [see Warnings and Precautions (5.2)].

5 WARNINGS AND PRECAUTIONS

5.1 Not for Acute Use

SPIRIVA RESPIMAT is intended as a once-daily maintenance treatment for COPD and asthma and should not be used for the relief of acute symptoms, i.e., as rescue therapy for the treatment of acute episodes of bronchospasm. In the event of an acute attack, a rapid-acting beta2-agonist should be used.

5.2 Immediate Hypersensitivity Reactions

Immediate hypersensitivity reactions, including urticaria, angioedema (including swelling of the lips, tongue or throat), rash, bronchospasm, anaphylaxis, or itching may occur after administration of SPIRIVA RESPIMAT. If such a reaction occurs, therapy with SPIRIVA RESPIMAT should be stopped at once and alternative treatments should be considered. Given the similar structural formula of atropine to tiotropium, patients with a history of hypersensitivity reactions to atropine or its derivatives should be closely monitored for similar hypersensitivity reactions to SPIRIVA RESPIMAT.

5.3 Paradoxical Bronchospasm

Inhaled medicines, including SPIRIVA RESPIMAT, may cause paradoxical bronchospasm. If this occurs, it should be treated immediately with an inhaled short-acting beta2-agonist such as albuterol. Treatment with SPIRIVA RESPIMAT should be stopped and other treatments considered.

5.4 Worsening of Narrow-Angle Glaucoma

SPIRIVA RESPIMAT should be used with caution in patients with narrow-angle glaucoma. Prescribers and patients should be alert for signs and symptoms of acute narrow-angle glaucoma (e.g., eye pain or discomfort, blurred vision, visual halos or colored images in association with red eyes from conjunctival congestion and corneal edema). Instruct patients to consult a physician immediately should any of these signs or symptoms develop.

5.5 Worsening of Urinary Retention

SPIRIVA RESPIMAT should be used with caution in patients with urinary retention. Prescribers and patients should be alert for signs and symptoms of urinary retention (e.g., difficulty passing urine, painful urination), especially in patients with prostatic hyperplasia or bladder-neck obstruction. Instruct patients to consult a physician immediately should any of these signs or symptoms develop.

5.6 Renal Impairment

As a predominantly renally excreted drug, patients with moderate to severe renal impairment (creatinine clearance of <60 mL/min) treated with SPIRIVA RESPIMAT should be monitored closely for anticholinergic side effects [see Clinical Pharmacology (12.3)].

6 ADVERSE REACTIONS

The following adverse reactions are described, or described in greater detail, in other sections:

- Immediate hypersensitivity reactions [see Warnings and Precautions (5.2)]
- Paradoxical bronchospasm [see Warnings and Precautions (5.3)]
- Worsening of narrow-angle glaucoma [see Warnings and Precautions (5.4)]
- Worsening of urinary retention [see Warnings and Precautions (5.5)]

Because clinical trials are conducted under widely varying conditions, the incidence of adverse reactions observed in the clinical trials of a drug cannot be directly compared to the incidences in the clinical trials of another drug and may not reflect the incidences observed in practice.

Since the same active ingredient (tiotropium bromide) is administered to COPD and asthma patients, prescribers and patients should take into account that the observed adverse reactions could be relevant for both patient populations independent of dosage strength.

6.1 Clinical Trials Experience in Chronic Obstructive Pulmonary Disease

The SPIRIVA RESPIMAT clinical development program included ten placebo controlled clinical trials in COPD. Two trials were four-week cross-over trials and eight were parallel group trials. The parallel group trials included a three-week dose-ranging trial, two 12-week trials, three 48-week trials, and two trials of 4-week and 24-week duration conducted for a different program that contained tiotropium bromide 5 mcg treatment arms. The primary safety database consists of pooled data from the 7 randomized, parallel-group, double-blind, placebo-controlled studies of 4-48 weeks in treatment duration. These trials included 6,565 adult COPD patients (75% males and 25% females) 40 years of age and older. Of these patients, 3,282 patients were treated with SPIRIVA RESPIMAT 5 mcg and 3,283 received placebo. The SPIRIVA RESPIMAT 5 mcg group was composed mostly of Caucasians (78%) with a mean age of 65 years and a mean baseline percent predicted post-bronchodilator FEV1 of 46%.

In these 7 clinical trials, 68.3% of patients exposed to SPIRIVA RESPIMAT 5 mcg reported an adverse event compared to 68.7% of patients in the placebo group. There were 68 deaths in the SPIRIVA RESPIMAT 5 mcg treatment group (2.1%) and 52 deaths (1.6%) in patients who received placebo [see Clinical Studies (14) Long-term Active-Controlled Mortality Trial: Survival]. The percentage of SPIRIVA RESPIMAT patients who discontinued due to an adverse event were 7.3% compared to 10% with placebo patients. The percentage of SPIRIVA RESPIMAT 5 mcg patients who experienced a serious adverse event were 15.0% compared to 15.1% with placebo patients. In both groups, the adverse event most commonly leading to discontinuation was COPD exacerbation (SPIRIVA RESPIMAT 2.0%, placebo 4.0%) which was also the most frequent serious adverse event. The most commonly reported adverse reactions were pharyngitis, cough, dry mouth, and sinusitis (Table 1). Other adverse reactions reported in individual patients and consistent with possible anticholinergic effects included constipation, dysuria, and urinary retention.

Table 1 shows all adverse reactions that occurred with an incidence of >3% in the SPIRIVA RESPIMAT 5 mcg treatment group, and a higher incidence rate on SPIRIVA RESPIMAT 5 mcg than on placebo.

Table 1 Number (Percentage) of COPD Patients Exposed to SPIRIVA RESPIMAT 5 mcg with Adverse Reactions >3% (and Higher than Placebo): Pooled Data from 7 Clinical Trials with Treatment Periods Ranging between 4 and 48 Weeks in COPD Patients
Body System (Reaction)* | SPIRIVA RESPIMAT 5 mcg [n=3,282] | Placebo [n=3,283]
Gastrointestinal Disorders
Dry mouth | 134 (4.1) | 52 (1.6)
Infections and Infestations
Pharyngitis | 378 (11.5) | 333 (10.1)
Respiratory, Thoracic, and Mediastinal Disorders
Cough | 190 (5.8) | 182 (5.5)
Sinusitis | 103 (3.1) | 88 (2.7)
*Adverse reactions include a grouping of similar terms

Other reactions that occurred in the SPIRIVA RESPIMAT 5 mcg group at an incidence of 1% to 3% and at a higher incidence rate on SPIRIVA RESPIMAT 5 mcg than on placebo included: Cardiac disorders: palpitations; Gastrointestinal disorders: constipation, gastroesophageal reflux disease, oropharyngeal candidiasis; Nervous system disorders: dizziness; Respiratory, thoracic, and mediastinal disorders: dysphonia; Skin and subcutaneous tissue disorders: pruritus, rash; Renal and urinary disorders: urinary tract infection.

Less Common Adverse Reactions

Among the adverse reactions observed in the clinical trials with an incidence of <1% and at a higher incidence rate on SPIRIVA RESPIMAT 5 mcg than on placebo were: dysphagia, gingivitis, intestinal obstruction including ileus paralytic, joint swelling, dysuria, urinary retention, epistaxis, laryngitis, angioedema, dry skin, skin infection, and skin ulcer.

6.2 Clinical Trials Experience in Asthma

Adult Patients

SPIRIVA RESPIMAT 2.5 mcg has been compared to placebo in four placebo-controlled parallel-group trials ranging from 12 to 52 weeks of treatment duration in adult patients (aged 18 to 75 years) with asthma. The safety data described below are based on one 1-year, two 6-month and one 12-week randomized, double-blind, placebo-controlled trials in a total of 2,849 asthma patients on background treatment of at least ICS or ICS and long-acting beta agonist (ICS/LABA). Of these patients, 787 were treated with SPIRIVA RESPIMAT at the recommended dosage of 2.5 mcg once-daily; 59.7% were female and 47.5% were Caucasian with a mean age of 43.7 years and a mean post-bronchodilator percent predicted forced expiratory volume in 1 second (FEV1) of 90.0% at baseline.

Table 2 shows all adverse reactions that occurred with an incidence of >2% in the SPIRIVA RESPIMAT 2.5 mcg treatment group, and a higher incidence rate on SPIRIVA RESPIMAT 2.5 mcg than on placebo.

Table 2 Number (Percentage) of Asthma Patients Exposed to SPIRIVA RESPIMAT 2.5 mcg with Adverse Reactions >2% (and Higher than Placebo): Pooled Data from 4 Adult Clinical Trials with Treatment Periods Ranging between 12 and 52 Weeks in Asthma Patients
Body System (Reaction)* | SPIRIVA RESPIMAT 2.5 mcg [n=787] | Placebo [n=735]
Respiratory, Thoracic, and Mediastinal Disorders
Pharyngitis | 125 (15.9) | 91 (12.4)
Sinusitis | 21 (2.7) | 10 (1.4)
Bronchitis | 26 (3.3) | 10 (1.4)
Nervous System Disorders
Headache | 30 (3.8) | 20 (2.7)
*Adverse reactions include a grouping of similar terms

Other reactions that occurred in the SPIRIVA RESPIMAT 2.5 mcg group at an incidence of 1% to 2% and at a higher incidence rate on SPIRIVA RESPIMAT 2.5 mcg than on placebo included: Nervous system disorders: dizziness; Gastrointestinal disorders: oropharyngeal candidiasis, diarrhea; Respiratory, thoracic, and mediastinal disorders: cough, rhinitis allergic; Renal and urinary disorders: urinary tract infection; General disorders and administration site conditions: pyrexia; and Vascular disorders: hypertension.

Less Common Adverse Reactions

Among the adverse reactions observed in the clinical trials with an incidence of 0.5% to <1% and at a higher incidence rate on SPIRIVA RESPIMAT 2.5 mcg than on placebo were: palpitations, dysphonia, acute tonsillitis, tonsillitis, rhinitis, herpes zoster, gastroesophageal reflux disease, oropharyngeal discomfort, abdominal pain upper, insomnia, hypersensitivity (including immediate reactions), angioedema, dehydration, arthralgia, muscle spasms, pain in extremity, chest pain, hepatic function abnormal, liver function test abnormal.

Adolescent Patients Aged 12 to 17 years

SPIRIVA RESPIMAT 2.5 mcg has been compared to placebo in two placebo-controlled parallel-group trials ranging from 12 to 48 weeks of treatment duration in adolescent patients with asthma. The safety data described below are based on one 48-week and one 12-week double-blind, placebo-controlled trials in a total of 789 adolescent asthma patients on background treatment of at least ICS or ICS plus one or more controller. Of these patients, 252 were treated with SPIRIVA RESPIMAT at the recommended dosage of 2.5 mcg once-daily; 63.9% were male and 95.6% were Caucasian with a mean age of 14.3 years and a mean post-bronchodilator percent predicted FEV1 of 98.3% at baseline. The adverse reaction profile for adolescent patients with asthma was comparable to that observed in adult patients with asthma.

Pediatric Patients Aged 6 to 11 years

SPIRIVA RESPIMAT 2.5 mcg has been compared to placebo in two placebo-controlled parallel-group trials ranging from 12 to 48 weeks of treatment duration in pediatric patients aged 6 to 11 years with asthma. The safety data are based on one 48-week and one 12-week double-blind, placebo-controlled trials in a total of 801 pediatric asthma patients aged 6 to 11 years on background treatment of at least ICS or ICS plus one or more controller. Of these patients, 271 were treated with SPIRIVA RESPIMAT at the recommended dose of 2.5 mcg once-daily; 71.2% were male and 86.7% were Caucasian with a mean age of 8.9 years and a mean post-bronchodilator percent predicted FEV1 of 97.9% at baseline. The adverse reaction profile for pediatric patients aged 6 to 11 years with asthma was comparable to that observed in adult patients with asthma.

SPIRIVA RESPIMAT 5 mcg also has been compared to placebo in seven placebo-controlled parallel-group trials ranging from 12 to 52 weeks of treatment duration in 4,149 adult patients (aged 18 to 75 years) with asthma and in two placebo-controlled parallel-group trials ranging from 12 to 48 weeks of treatment duration in 789 adolescent patients (1,370 adults and 264 adolescents receiving SPIRIVA RESPIMAT 5 mcg once-daily). The adverse reaction profile for SPIRIVA RESPIMAT 5 mcg in patients with asthma was comparable to that observed with SPIRIVA RESPIMAT 2.5 mcg in patients with asthma.

6.3 Postmarketing Experience

In addition to the adverse reactions observed during the SPIRIVA RESPIMAT clinical trials in COPD, the following adverse reactions have been observed during post-approval use of SPIRIVA RESPIMAT 5 mcg and another tiotropium formulation, SPIRIVA® HandiHaler® (tiotropium bromide inhalation powder). Because these reactions are reported voluntarily from a population of uncertain size, it is not always possible to reliably estimate their frequency or establish a causal relationship to drug exposure.

- Glaucoma, intraocular pressure increased, vision blurred,
- Atrial fibrillation, tachycardia, supraventricular tachycardia,
- Bronchospasm,
- Glossitis, stomatitis,
- Dehydration,
- Insomnia,
- Hypersensitivity (including immediate reactions), and urticaria.

7 DRUG INTERACTIONS

7.1 Concomitant Respiratory Medications

SPIRIVA RESPIMAT has been used concomitantly with short-acting and long-acting sympathomimetic (beta-agonists) bronchodilators, methylxanthines, oral and inhaled steroids, antihistamines, mucolytics, leukotriene modifiers, cromones, and anti-IgE treatment without increases in adverse reactions.

7.2 Anticholinergics

There is potential for an additive interaction with concomitantly used anticholinergic medications. Therefore, avoid coadministration of SPIRIVA RESPIMAT with other anticholinergic-containing drugs as this may lead to an increase in anticholinergic adverse effects [see Warnings and Precautions (5.4, 5.5) and Adverse Reactions (6)].

8 USE IN SPECIFIC POPULATIONS

8.1 Pregnancy

Risk Summary

The limited human data with SPIRIVA RESPIMAT use during pregnancy are insufficient to inform a drug-associated risk of adverse pregnancy-related outcomes. There are risks to the mother and the fetus associated with poorly controlled asthma in pregnancy (see Clinical Considerations). Based on animal reproduction studies, no structural abnormalities were observed when tiotropium was administered by inhalation to pregnant rats and rabbits during the period of organogenesis at doses 790 and 8 times, respectively, the maximum recommended human daily inhalation dose (MRHDID). Increased post-implantation loss was observed in rats and rabbits administered tiotropium at maternally toxic doses 430 times and 40 times the MRHDID, respectively (see Data).

The estimated background risk of major birth defects and miscarriage for the indicated population is unknown. All pregnancies have a background risk of birth defect, loss or other adverse outcomes. In the U.S. general population, the estimated background risk of major birth defects and miscarriage in clinically recognized pregnancies is 2% to 4% and 15% to 20%, respectively.

Clinical Considerations

Disease-Associated Maternal and/or Embryo-Fetal Risk

Poorly or moderately controlled asthma in pregnancy increases the maternal risk of preeclampsia and infant prematurity, low birth weight, and small for gestational age. The level of asthma control should be closely monitored in pregnant women and treatment adjusted as necessary to maintain optimal control.

Data

Animal Data

In 2 separate embryo-fetal development studies, pregnant rats and rabbits received tiotropium during the period of organogenesis at doses up to approximately 790 and 8 times the maximum recommended human daily inhalation dose (MRHDID), respectively (on a mcg/m^2 basis at inhalation doses of 1,471 and 7 mcg/kg/day in rats and rabbits, respectively). No evidence of structural abnormalities was observed in rats or rabbits. However, in rats, tiotropium caused fetal resorption, litter loss, decreases in the number of live pups at birth and the mean pup weights, and a delay in pup sexual maturation at tiotropium doses of approximately 40 times the MRHDID (on a mcg/m^2 basis at a maternal inhalation dose of 78 mcg/kg/day). In rabbits, tiotropium caused an increase in post-implantation loss at a tiotropium dose of approximately 430 times the MRHDID (on a mcg/m^2 basis at a maternal inhalation dose of 400 mcg/kg/day). Such effects were not observed at approximately 5 and 95 times the MRHDID, respectively (on a mcg/m^2 basis at inhalation doses of 9 and 88 mcg/kg/day in rats and rabbits, respectively).

8.2 Lactation

Risk Summary

There are no data on the presence of tiotropium in human milk, the effects on the breastfed infant, or the effects on milk production. Tiotropium is present in milk of lactating rats; however, due to species-specific differences in lactation physiology, the clinical relevance of these data are not clear (see Data). The developmental and health benefits of breastfeeding should be considered along with the mother's clinical need for SPIRIVA RESPIMAT and any potential adverse effects on the breastfed child from SPIRIVA RESPIMAT or from the underlying maternal condition.

Data

The distribution of tiotropium bromide into milk was investigated after a single intravenous administration of 10 mg/kg to lactating rats. Tiotropium and/or its metabolites are present in the milk of lactating rats at concentrations above those in plasma.

8.4 Pediatric Use

The safety and efficacy of SPIRIVA RESPIMAT 2.5 mcg have been established in pediatric patients aged 6 to 17 years with asthma in 6 clinical trials up to 1 year in duration. In three clinical trials, 327 patients aged 12 to 17 years with asthma were treated with SPIRIVA RESPIMAT 2.5 mcg; in three additional clinical trials, 345 patients aged 6 to 11 years with asthma were treated with SPIRIVA RESPIMAT 2.5 mcg. Patients in these age groups demonstrated efficacy results similar to those observed in patients aged 18 years and older with asthma [see Clinical Studies (14.2)].

The safety and efficacy of SPIRIVA RESPIMAT have not been established in pediatric patients less than 6 years of age. The safety of SPIRIVA RESPIMAT 2.5 mcg has been studied in pediatric patients with asthma aged 1 to 5 years who were on background treatment of at least ICS in one placebo-controlled clinical trial of 12 weeks duration (36 treated with SPIRIVA RESPIMAT 2.5 mcg and 34 with placebo RESPIMAT). In this study, SPIRIVA RESPIMAT or placebo RESPIMAT was delivered with the AeroChamber Plus Flow-Vu® valved holding chamber with facemask once daily. The majority of the patients in the trial were male (60.4%) and Caucasian (76.2%) with a mean age of 3.1 years. The adverse reaction profile was similar to that observed in adults and older pediatric patients [see Adverse Reactions (6.2)].

In Vitro Characterization Studies with Valved Holding Chamber

Dose delivery and fine particle fraction of SPIRIVA RESPIMAT when administered via a valved holding chamber (AeroChamber Plus Flow-Vu® with or without face mask) was assessed by in vitro studies.

Inspiratory flow rates of 4.9, 8.0, and 12.0 L/min in combination with holding times of 0, 2, 5, and 10 seconds were tested. The flow rates were selected to be representative of inspiratory flow rates of children aged 6 to 12 months, 2 to 5 years, and over 5 years, respectively.

Table 3 summarizes the results for delivered dose under the respective test conditions and configurations.

Table 3 In Vitro Medication Delivery through AeroChamber Plus Flow-Vu® Valved Holding Chamber with Face Mask at Different Flow Rates and Holding Times Using the Dose 2.5 mcg (as two actuations)
Flow Rate (L/min) and corresponding age | Mask | Holding Time (seconds) | Mean Medication Delivery through AeroChamber Plus Flow-Vu® per Dose (mcg) | Body Weight 50th Percentile (kg)a | Medication Delivered per Dose (ng/kg)b
4.9 (6 to 12 Months) | small | 0 2 5 10 | 0.85 0.86 0.55 0.62 | 7.5-9.9 | 86-113 87-115 56-73 63-83
8.0 (2 to 5 Years) | medium | 0 2 5 10 | 0.74 0.93 0.72 0.57 | 12.3-18.0 | 41-60 52-76 40-59 32-46
12.0 (> 5 Years) | medium | 0 2 5 10 | 1.16 0.96 0.78 0.61 | 18.0 | 64 53 43 34
a Centers for Disease Control and Prevention growth charts, developed by the National Center for Health Statistics in collaboration with the National Center for Chronic Disease Prevention and Health Promotion (2009).
Body weight values correspond to the average of the 50 percentile weight for boys and girls at the ages indicated.
b Inhalation of SPIRIVA RESPIMAT 2.5 mcg dose (as two actuations) in a 70-kg adult without use of a valved holding chamber and mask delivers approximately 2.5 mcg, or 36 ng/kg.

The in vitro study data show a reduction of the absolute delivered dose through the valved holding chamber. However, in terms of dose per kilogram of body weight the data suggest that under all tested conditions the dose of SPIRIVA RESPIMAT delivered by the AeroChamber Plus Flow-Vu® valved holding chamber with mask will at least lead to a dosing comparable to that of adults without use of a holding chamber and mask (Table 3). The fine particle fraction (<5 µm) across the flow rates used in these studies was 69-89% of the delivered dose through the valved holding chamber, consistent with the removal of the coarser fraction by the holding chamber. In contrast, the fine particle fraction for SPIRIVA RESPIMAT delivered without a holding chamber typically represents approximately 60% of the delivered dose.

8.5 Geriatric Use

Based on available data, no adjustment of SPIRIVA RESPIMAT dosage in geriatric patients is warranted [see Clinical Pharmacology (12.3)].

Thirty nine percent of SPIRIVA RESPIMAT clinical trial patients with COPD were between 65 and 75 years of age and 14% were greater than or equal to 75 years of age. Approximately seven percent of SPIRIVA RESPIMAT clinical trial patients with asthma were greater than or equal to 65 years of age. The adverse drug reaction profiles were similar in the older population compared to the patient population overall.

8.6 Renal Impairment

Patients with moderate to severe renal impairment (creatinine clearance of <60 mL/min) treated with SPIRIVA RESPIMAT should be monitored closely for anticholinergic side effects [see Dosage and Administration (2), Warnings and Precautions (5.6), and Clinical Pharmacology (12.3)].

8.7 Hepatic Impairment

The effects of hepatic impairment on the pharmacokinetics of tiotropium were not studied.

10 OVERDOSAGE

High doses of tiotropium may lead to anticholinergic signs and symptoms. However, there were no systemic anticholinergic adverse effects following a single inhaled dose of up to 282 mcg tiotropium dry powder in 6 healthy volunteers. Dry mouth/throat and dry nasal mucosa occurred in a dose-dependent [10-40 mcg daily] manner, following 14-day dosing of up to 40 mcg tiotropium bromide inhalation solution in healthy subjects.

Treatment of overdosage consists of discontinuation of SPIRIVA RESPIMAT together with institution of appropriate symptomatic and/or supportive therapy.

11 DESCRIPTION

The active component of SPIRIVA RESPIMAT is tiotropium. The drug substance, tiotropium bromide monohydrate, is an anticholinergic with specificity for muscarinic receptors. It is chemically described as (1α, 2β, 4β, 5α, 7β)-7-[(Hydroxydi-2-thienylacetyl)oxy]-9,9-dimethyl-3-oxa-9-azoniatricyclo[3.3.1.0^2,4] nonane bromide monohydrate. It is a synthetic, non-chiral, quaternary ammonium compound. Tiotropium bromide is a white or yellowish white powder. It is sparingly soluble in water and soluble in methanol.

The structural formula is:

Tiotropium bromide (monohydrate) has a molecular mass of 490.4 and a molecular formula of C19H22NO4S2Br ∙ H2O.

The drug product, SPIRIVA RESPIMAT, is composed of a sterile, aqueous solution of tiotropium bromide filled into a 4.5 mL plastic container crimped into an aluminum cylinder (SPIRIVA RESPIMAT cartridge) for use with the SPIRIVA RESPIMAT inhaler. Excipients include benzalkonium chloride, edetate disodium, hydrochloric acid, and water for injection. The SPIRIVA RESPIMAT cartridge is only intended for use with the SPIRIVA RESPIMAT inhaler. The RESPIMAT inhaler is a hand held, pocket sized oral inhalation device that uses mechanical energy to generate a slow-moving aerosol cloud of medication from a metered volume of the drug solution.

When used with the SPIRIVA RESPIMAT inhaler, each cartridge containing 4 grams of sterile aqueous solution delivers the labeled number of metered actuations after preparation for use. Each dose (one dose equals two actuations) from the SPIRIVA RESPIMAT inhaler delivers 2.5 mcg or 5 mcg of tiotropium (equivalent to 3.124 mcg or 6.247 mcg, respectively, of tiotropium bromide monohydrate) in 22.1 mcL from the mouthpiece. As with all inhaled drugs, the actual amount of drug delivered to the lung may depend on patient factors, such as the coordination between the actuation of the inhaler and inspiration through the delivery system. The duration of inspiration should be at least as long as the spray duration (1.5 seconds).

Prior to first use, the SPIRIVA RESPIMAT cartridge is inserted into the SPIRIVA RESPIMAT inhaler and the unit is primed. When using the unit for the first time, patients are to actuate the inhaler toward the ground until an aerosol cloud is visible and then repeat the process three more times. The unit is then considered primed and ready for use. If not used for more than 3 days, patients are to actuate the inhaler once to prepare the inhaler for use. If not used for more than 21 days, patients are to actuate the inhaler until an aerosol cloud is visible and then repeat the process three more times to prepare the inhaler for use [see Patient Counseling Information (17)].

12 CLINICAL PHARMACOLOGY

12.1 Mechanism of Action

Tiotropium is a long-acting, antimuscarinic agent, which is often referred to as an anticholinergic. It has similar affinity to the subtypes of muscarinic receptors, M1 to M5. In the airways, it exhibits pharmacological effects through inhibition of M3-receptors at the smooth muscle leading to bronchodilation. The competitive and reversible nature of antagonism was shown with human and animal origin receptors and isolated organ preparations. In preclinical in vitro as well as in vivo studies, prevention of methacholine-induced bronchoconstriction effects was dose-dependent and lasted longer than 24 hours. The bronchodilation following inhalation of tiotropium is predominantly a site-specific effect.

12.2 Pharmacodynamics

Cardiac Electrophysiology

In a multicenter, randomized, double-blind trial using tiotropium dry powder for inhalation that enrolled 198 patients with COPD, the number of subjects with changes from baseline-corrected QT interval of 30 to 60 msec was higher in the SPIRIVA group as compared with placebo. This difference was apparent using both the Bazett (QTcB) [20 (20%) patients vs. 12 (12%) patients] and Fredericia (QTcF) [16 (16%) patients vs. 1 (1%) patient] corrections of QT for heart rate. No patients in either group had either QTcB or QTcF of >500 msec. Other clinical trials with SPIRIVA did not detect an effect of the drug on QTc intervals.

The effect of tiotropium dry powder for inhalation on QT interval was also evaluated in a randomized, placebo- and positive-controlled crossover study in 53 healthy volunteers. Subjects received tiotropium inhalation powder 18 mcg, 54 mcg (3 times the recommended dose), or placebo for 12 days. ECG assessments were performed at baseline and throughout the dosing interval following the first and last dose of study medication. Relative to placebo, the maximum mean change from baseline in study-specific QTc interval was 3.2 msec and 0.8 msec for tiotropium inhalation powder 18 mcg and 54 mcg, respectively. No subject showed a new onset of QTc >500 msec or QTc changes from baseline of ≥60 msec.

12.3 Pharmacokinetics

Tiotropium is administered as an inhalation spray. Some of the pharmacokinetic data described below were obtained with higher doses than recommended for therapy. A dedicated pharmacokinetic study in patients with COPD evaluating once-daily tiotropium delivered from the RESPIMAT inhaler (5 mcg) and as inhalation powder (18 mcg) from the HandiHaler resulted in a similar systemic exposure between the two products.

Absorption

Following inhalation of the solution by young healthy volunteers, urinary excretion data suggests that approximately 33% of the inhaled dose reaches the systemic circulation. Oral solutions of tiotropium have an absolute bioavailability of 2% to 3%. Food is not expected to influence the absorption of tiotropium for the same reason. Following 4-week SPIRIVA RESPIMAT once daily dosing, maximum tiotropium plasma concentrations were observed 5-7 minutes after inhalation in COPD and asthma patients.

Distribution

The drug has a plasma protein binding of 72% and shows a volume of distribution of 32 L/kg after an intravenous dose to young healthy volunteers. Local concentrations in the lung are not known, but the mode of administration suggests substantially higher concentrations in the lung. Studies in rats have shown that tiotropium does not penetrate the blood-brain barrier.

Elimination

Metabolism

The extent of metabolism is small. This is evident from a urinary excretion of 74% of unchanged substance after an intravenous dose to young healthy volunteers. Tiotropium, an ester, is nonenzymatically cleaved to the alcohol N-methylscopine and dithienylglycolic acid, neither of which binds to muscarinic receptors.

In vitro experiments with human liver microsomes and human hepatocytes suggest that a fraction of the administered dose (74% of an intravenous dose is excreted unchanged in the urine, leaving 25% for metabolism) is metabolized by cytochrome P450-dependent oxidation and subsequent glutathione conjugation to a variety of Phase II metabolites. This enzymatic pathway can be inhibited by CYP450 2D6 and 3A4 inhibitors, such as quinidine, ketoconazole, and gestodene. Thus, CYP450 2D6 and 3A4 are involved in the metabolic pathway that is responsible for the elimination of a small part of the administered dose. In vitro studies using human liver microsomes showed that tiotropium in supra-therapeutic concentrations does not inhibit CYP450 1A1, 1A2, 2B6, 2C9, 2C19, 2D6, 2E1, or 3A4.

Excretion

The terminal half-life of tiotropium in COPD and asthma patients following once daily inhalation is 25 and 44 hours, respectively. Total clearance was 880 mL/min after an intravenous dose in young healthy volunteers. Intravenously administered tiotropium bromide is mainly excreted unchanged in urine (74%). Following 21-day once daily inhalation of 5 mcg of the solution by patients with COPD, 24-hour urinary excretion is 18.6% (0.93 mcg) of the dose. The renal clearance of tiotropium exceeds the creatinine clearance, indicating secretion into the urine. In comparison, 12.8% (0.32 mcg) of the dose was excreted unchanged in the urine over 24 hours at steady state after inhalation of 2.5 mcg in patients with asthma. After chronic once-daily inhalation by COPD and asthma patients, pharmacokinetic steady-state was reached by day 7 with no accumulation thereafter.

Specific Populations

Geriatric Patients

As expected for all predominantly renally excreted drugs, advancing age was associated with a decrease of tiotropium renal clearance (347 mL/min in COPD patients <65 years to 275 mL/min in COPD patients ≥65 years). This did not result in a corresponding increase in AUC0-6,ss and Cmax,ss values following inhalation of the solution. Exposure to tiotropium was not found to differ with age in patients with asthma.

Pediatric Patients

The peak and total exposure to tiotropium was not found to differ between pediatric patients (aged 6 to 17 years) and adults with asthma.

Renal Impairment

Following 4-week SPIRIVA RESPIMAT 5 mcg once daily dosing in patients with COPD, mild renal impairment (creatinine clearance 60 - <90 mL/min) resulted in 23% higher AUC0-6,ss and 17% higher Cmax,ss values; moderate renal impairment (creatinine clearance 30 - <60 mL/min) resulted in 57% higher AUC0-6,ss and 31% higher Cmax,ss values compared to COPD patients with normal renal function (creatinine clearance ≥90 mL/min). The influence of mild or moderate renal impairment on the systemic exposure to SPIRIVA RESPIMAT 2.5 mcg in patients with asthma was similar to what has been described for COPD above. There lacks sufficient data of tiotropium exposure in patients with severe renal impairment (creatinine clearance <30 mL/min) following inhalation of SPIRIVA RESPIMAT. However AUC0-4 and Cmax were 94% and 52% higher, respectively, in patients with severe renal impairment following intravenous infusion of tiotropium bromide.

Hepatic Impairment

The effects of hepatic impairment on the pharmacokinetics of tiotropium were not studied.

Drug Interactions

An interaction study with tiotropium (14.4 mcg intravenous infusion over 15 minutes) and cimetidine 400 mg three times daily or ranitidine 300 mg once-daily was conducted. Concomitant administration of cimetidine with tiotropium resulted in a 20% increase in the AUC0-4h, a 28% decrease in the renal clearance of tiotropium and no significant change in the Cmax and amount excreted in urine over 96 hours. Co-administration of tiotropium with ranitidine did not affect the pharmacokinetics of tiotropium.

Common concomitant medications (LABA, ICS) used by patients with COPD were not found to alter the exposure to tiotropium. Similarly, common concomitant medications (LABA, ICS+LABA combinations, oral corticosteroids and leukotriene modifiers) used by patients with asthma were not found to alter the exposure to tiotropium.

13 NONCLINICAL TOXICOLOGY

13.1 Carcinogenesis, Mutagenesis, Impairment of Fertility

No evidence of tumorigenicity was observed in a 104-week inhalation study in rats at tiotropium doses up to 59 mcg/kg/day, in an 83-week inhalation study in female mice at doses up to 145 mcg/kg/day, and in a 101-week inhalation study in male mice at doses up to 2 mcg/kg/day. These doses correspond to approximately 30, 40, and 0.5, times the maximum recommended human daily inhalation dose (MRHDID) on a mcg/m^2 basis, respectively.

Tiotropium bromide demonstrated no evidence of mutagenicity or clastogenicity in the following assays: the bacterial gene mutation assay, the V79 Chinese hamster cell mutagenesis assay, the chromosomal aberration assays in human lymphocytes in vitro and mouse micronucleus formation in vivo, and the unscheduled DNA synthesis in primary rat hepatocytes in vitro assay.

In rats, decreases in the number of corpora lutea and the percentage of implants were noted at inhalation tiotropium doses of 78 mcg/kg/day or greater (approximately 40 times the MRHDID on a mcg/m^2 basis). No such effects were observed at 9 mcg/kg/day (approximately 5 times the MRHDID on a mcg/m^2 basis). The fertility index, however, was not affected at inhalation doses up to 1,689 mcg/kg/day (approximately 910 times the MRHDID on a mcg/m^2 basis).

14 CLINICAL STUDIES

14.1 Chronic Obstructive Pulmonary Disease

The efficacy of SPIRIVA RESPIMAT compared to placebo was evaluated in 6 clinical trials: one dose-ranging trial and 5 confirmatory trials (Trials 1-5). In addition, SPIRIVA RESPIMAT was compared to SPIRIVA HandiHaler in a long-term active-controlled trial in COPD (Trial 6).

Dose-Ranging Trial

Dose selection for the Phase III clinical program was supported by a 3-week randomized, double-blind, placebo and active-controlled, parallel group trial in 202 COPD patients. A total of five doses of tiotropium RESPIMAT (1.25 to 20 mcg) were evaluated compared to placebo. Results demonstrated numerical improvements in FEV1 at all doses compared to placebo. The difference in trough FEV1 from placebo for the 1.25, 2.5, 5, 10 and 20 mcg once daily doses were 0.08 L (95% CI -0.03, 0.20), 0.03 L (-0.08, 0.15), 0.13 L (0.02, 0.25), 0.11 L (-0.004, 0.224), and 0.13 L (0.01, 0.24), respectively. Based on these results, the 5 and 10 mcg doses were further evaluated in the confirmatory COPD trials.

Confirmatory Trials

A total of 6,614 COPD patients (2,801 receiving SPIRIVA RESPIMAT 5 mcg and 2,798 receiving placebo) were studied in the five confirmatory trials of SPIRIVA RESPIMAT. Trials 1 and 2 were 12-week, randomized, double-blind, placebo- and active- (ipratropium) controlled trials that evaluated bronchodilation. Trials 3-5 were 48-week, randomized, double-blind, placebo-controlled, trials that evaluated bronchodilation and effects on COPD exacerbations. Trials 1-4 included both the tiotropium RESPIMAT 5 mcg and 10 mcg doses, whereas Trial 5 included only the 5 mcg dose. These trials enrolled patients who had a clinical diagnosis of COPD, were 40 years of age or older, had a history of smoking greater than 10 pack-years, had an FEV1 less than or equal to 60% of predicted and a ratio of FEV1/FVC of less than or equal to 0.7. All treatments were administered once-daily in the morning. Change from baseline in trough FEV1 was a primary endpoint in all trials. Trials 3-5 included COPD exacerbations as primary endpoints.

Baseline patient characteristics were similar across the five individual confirmatory trials, except for race in Trial 5 in which there were more Asian patients (30%) compared to other trials (<1%). The mean age ranged from 62 to 66 years. Most patients were male (64-78%), ex-smokers (57-65%) and Caucasian (69-99%). Mean pre-bronchodilator FEV1 was between 1.03 and 1.26 L with a mean FEV1/FVC ratio of 42-50%. Except for LABAs and other inhaled anticholinergic agents, other pulmonary medications were allowed as concomitant therapy in Trials 1-4. LABA use was permitted in Trial 5.

Effect on Lung Function

SPIRIVA RESPIMAT 5 mcg demonstrated significant improvement in trough FEV1 compared to placebo in all 5 confirmatory trials (Table 4). The change from baseline in trough FEV1 over time from Trial 4 is depicted in Figure 1 and is representative of the other two 48-week trials. In Trials 3 and 4 patients treated with SPIRIVA RESPIMAT 5 mcg also used less rescue medication compared to patients on placebo.

Table 4 Mean Change from Baseline in Trough FEV1 (L) at End of Treatment
Trial | SPIRIVA RESPIMAT 5 mcg N | Placebo N | Trough FEV1 (L) at End of Treatment Difference from placebo (95% CI)
Trial 1† | 85 | 87 | 0.11 (0.04, 0.18)
Trial 2† | 90 | 84 | 0.13 (0.07, 0.18)
Trial 3‡ | 326 | 296 | 0.14 (0.10, 0.18)
Trial 4‡ | 324 | 307 | 0.11 (0.08, 0.15)
Trial 5‡ | 1,889 | 1,870 | 0.10 (0.09, 0.12)
† at week 12
‡ at week 48

Figure 1 Trough FEV1 Change from Baseline over 48 weeks (Trial 4), SPIRIVA RESPIMAT 5 mcg

Exacerbations

Trials 3, 4, and 5 also evaluated the effect of SPIRIVA RESPIMAT 5 mcg on COPD exacerbations. For Trials 3 and 4, a pooled analysis of exacerbation rate per patient year was pre-specified as a primary endpoint, while the primary endpoint for Trial 5 was time to first exacerbation. Trial 5 also included exacerbation rate per patient year as a secondary endpoint. Exacerbations were defined as a complex of respiratory events/symptoms with a duration of ≥3 days with ≥2 of the following (increase of symptoms or new onset): shortness of breath/dyspnea/shallow, rapid breathing; sputum production (volume); occurrence of purulent sputum; cough; wheezing; chest tightness.

In the pooled analysis of Trials 3 and 4, SPIRIVA RESPIMAT 5 mcg significantly reduced the number of COPD exacerbations compared to placebo with 0.78 exacerbations/patient year versus 1.0 exacerbations/patient year, respectively, with a rate ratio of 0.78 (95% CI 0.67, 0.92). Time to first exacerbation was also delayed in SPIRIVA RESPIMAT 5 mcg patients. For Trial 5, in addition to the definition above, an exacerbation also had to result in a change in or requirement of treatment. In Trial 5, treatment with SPIRIVA RESPIMAT 5 mcg delayed the time to first COPD exacerbation compared to treatment with placebo [hazard ratio of 0.69 (95% CI 0.63, 0.77)]. Consistent with the pooled analysis of Trials 3 and 4, for Trial 5, exacerbation rate was also lower in SPIRIVA RESPIMAT 5 mcg compared to placebo. In Trial 5, SPIRIVA RESPIMAT 5 mcg also reduced the risk of COPD exacerbation-related hospitalization (HR = 0.73; 95% CI = 0.59, 0.90) compared to placebo.

Long-term Active-Controlled Mortality Trial

Survival

In a pooled analysis of SPIRIVA RESPIMAT placebo-controlled clinical trials with complete vital status (mortality) follow-up, including the three 48-week trials (Trial 3, 4, and 5) and one 24-week placebo-controlled trial, 68 deaths (Incidence Rate 2.64 deaths per 100 patient years) were observed in the SPIRIVA RESPIMAT 5 mcg treatment group compared to 51 deaths (Incidence Rate 1.98 deaths per 100 patient years) in those treated with placebo. In a 4-year, randomized, double-blind, placebo-controlled, multicenter clinical trial of tiotropium bromide inhalation powder (SPIRIVA HandiHaler) in 5,992 COPD patients a similar incidence rate of death had been observed between SPIRIVA HandiHaler and placebo treated groups.

For clarification of the observed difference in fatal events, a long-term, randomized, double-blind, double dummy, active-controlled trial with an observation period up to 3 years was conducted to evaluate the risk of all-cause mortality associated with the use of SPIRIVA RESPIMAT compared to SPIRIVA HandiHaler (Trial 6). The objective of this trial was to rule out a relative excess mortality risk of 25% for SPIRIVA RESPIMAT versus SPIRIVA HandiHaler. The primary endpoints were all-cause mortality and time to first COPD exacerbation. Trial 6 also included a lung function sub-study which measured trough FEV1 measured every 24 weeks for 120 weeks (461 patients receiving SPIRIVA RESPIMAT 5 mcg, 445 patients receiving SPIRIVA HandiHaler).

In Trial 6, 5,711 patients received SPIRIVA RESPIMAT 5 mcg and 5,694 patients received SPIRIVA HandiHaler. All patients were followed for vital status (mortality) at the end of the trial. At baseline, patient characteristics were balanced between the two treatment arms. The mean age was 65 years and approximately 70% of subjects were male. Approximately, 82% of patients were Caucasian, 14% were Asian, and 2% were Black. Mean post-bronchodilator FEV1 was 1.34 L with a mean FEV1/FVC ratio of 50%. The majority of patients were GOLD II or III (48% and 40%, respectively).

The vital status was confirmed in 99.7% of patients. The median exposure to treatment was 835 days for both treatment groups. All-cause mortality was similar between SPIRIVA RESPIMAT 5 mcg and SPIRIVA HandiHaler with an estimated hazard ratio of 0.96 [(95% CI of (0.84 to 1.09), Table 5].

Table 5 All-cause Mortality of SPIRIVA RESPIMAT vs SPIRIVA HandiHaler (Trial 6)
 | SPIRIVA RESPIMAT 5 mcg (N = 5,711) | SPIRIVA HandiHaler (N = 5,694)
Number (%) of Deaths | 423 (7.4) | 439 (7.7)
Incidence Rate per 100 patient years | 3.22 | 3.36
HR (95% CI)a | 0.96 (0.84, 1.09)
a Hazard ratios were estimated from a Cox proportional hazard model.

Cause of death was adjudicated by a blinded, independent committee. Cardiovascular deaths included cardiac death, sudden cardiac death, and sudden death; as well as fatal events caused by a cardiac disorder, vascular disorder, or stroke. There were 113 patients (2%) treated with SPIRIVA RESPIMAT 5 mcg who had cardiovascular deaths compared to 101 (2%) patients treated with SPIRIVA HandiHaler. Of the cardiovascular deaths, 11 (0.2%) and 3 (0.1%) deaths were due to myocardial infarction in SPIRIVA RESPIMAT 5 mcg patients and SPIRIVA HandiHaler patients, respectively. For cardiac deaths, sudden cardiac death, and sudden death, there were a total of 69 (1.2%) and 68 (1.2%) deaths in SPIRIVA RESPIMAT 5 mcg patients and SPIRIVA HandiHaler patients, respectively.

Effect on Lung Function and Exacerbations

In the lung function sub-study the effect of SPIRIVA RESPIMAT 5 mcg on trough FEV1 over 120 weeks was similar to SPIRIVA HandiHaler with a mean difference of -0.010 L (95% CI -0.038 to 0.018 L).

Trial 6 also included time to first exacerbation as a co-primary endpoint (exacerbations defined as in Trials 3-5). SPIRIVA RESPIMAT 5 mcg failed to demonstrate superiority to SPIRIVA HandiHaler with a similar time to first COPD exacerbation between treatment groups [hazard ratio of 0.98 (95% CI 0.93 to 1.03)].

14.2 Asthma

The SPIRIVA RESPIMAT clinical development program included six 4-week to 8-week cross-over design trials and ten 12-week to 48-week parallel-arm design trials in adult, adolescent (aged 12 to 17 years) and pediatric (aged 1 to 11 years) patients with asthma symptomatic on at least ICS. In all trials, SPIRIVA RESPIMAT was administered on a background of ICS therapy.

Dose Selection

Dose selection for the confirmatory trials was based on three randomized, double-blind, placebo-controlled, 4-week to 8-week, cross-over trials in 256 adult patients, 105 adolescent (age 12 to 17 years) patients, and 101 pediatric (age 6 to 11 years) patients that assessed doses ranging from 1.25 mcg to 10 mcg once daily. Results demonstrated numerical improvements in FEV1 at all doses compared to placebo; however, across the trials, the response was not dose-ordered. For adult patients, in the 4-week trial the difference in peak FEV1 within 3 h post-dosing (peak FEV1, 0-3hr) from placebo for the tiotropium RESPIMAT 1.25, 2.5, and 5 mcg doses were 0.138 L (95% CI 0.090, 0.186), 0.128 L (0.080, 0.176), and 0.188 L (0.140, 0.236), respectively. For adolescent patients, the difference in peak FEV1, 0-3hr from placebo for the tiotropium RESPIMAT 1.25, 2.5, and 5 mcg doses were 0.067 L (95% CI −0.005, 0.138), 0.057 L (−0.021, 0.135), and 0.113 L (0.036, 0.190), respectively. For pediatric patients, the difference in peak FEV1, 0-3h from placebo for the tiotropium RESPIMAT 1.25, 2.5, and 5 mcg doses were 0.075 L (95% CI, 0.030, 0.120), 0.104 L (0.059, 0.149), and 0.087 L (0.042, 0.132), respectively. The 10 mcg dose offered no substantial benefit over lower doses and resulted in more systemic anticholinergic side effects (e.g., dry mouth).

The two dose regimen trials in adults with asthma were randomized, double-blind, 4-week, cross-over trials comparing tiotropium RESPIMAT 2.5 mcg twice-daily with 5 mcg once-daily. 24-hour FEV1 results demonstrated comparable treatment effects for twice-daily and once-daily dosing.

12-week to 48-week Parallel-Arm Design Trials in Adults

The program for persistent asthma in adult patients included one 12-week (Trial 1), two replicate 24-week (Trials 2 and 3), and two replicate 48-week (Trials 4 and 5) randomized, double-blind, placebo-controlled trials in a total of 3,476 asthma patients (673 receiving SPIRIVA RESPIMAT 2.5 mcg once-daily, 1,128 receiving SPIRIVA RESPIMAT 5 mcg once-daily, 541 receiving salmeterol 50 mcg twice daily, and 1,134 receiving placebo) on background treatment of at least ICS. Trial 1 evaluated three treatments: SPIRIVA RESPIMAT 2.5 mcg once-daily, SPIRIVA RESPIMAT 5 mcg once-daily, and placebo. Trials 2 and 3 evaluated four treatments: SPIRIVA RESPIMAT 2.5 mcg once-daily, SPIRIVA RESPIMAT 5 mcg once-daily, salmeterol 50 mcg twice daily, and placebo. Trials 4 and 5 evaluated two treatments: SPIRIVA RESPIMAT 5 mcg once-daily and placebo. All trials enrolled patients who had a diagnosis of asthma, were 18 to 75 years of age, and were not current smokers. Patients enrolled in Trials 4 and 5 were required to have airway obstruction that was not fully reversible (post-bronchodilator FEV1/FVC, 0.70). The majority of the 3,476 patients in the adult asthma trials were female (60%), Caucasian (61%) or Asian (31%), and had never smoked (81%) with a mean age of 46 years. The patient characteristics for the 12 week to 48 week trials in adult patients with asthma are summarized in Table 6.

Table 6 Summary of Baseline Patient Characteristics, Adult Confirmatory Studies
 | Adults, 18 yrs and older
 | Trial 1 | Trial 2 | Trial 3 | Trial 4 | Trial 5
Demographics
Mean age in years (range) | 42.9 (18 – 74) | 43.3 (18 – 75) | 42.9 (18 – 75) | 53.4 (18-75) | 52.5 (19-75)
Mean duration of asthma (years) | 16.2 | 21.7 | 21.8 | 31.5 | 29.1
Smoking status, ex-smoker (%) | 18 | 14 | 19 | 22 | 26
Laboratory (median)
Absolute eosinophils (10^9/L) | 0.33 | 0.36 | 0.35 | 0.35 | 0.38
Total IgE (microgram/L) | 536 | 638 | 641 | 601 | 449
Pulmonary function test (mean)
Pre-bronchodilator FEV1 (L) | 2.30 | 2.18 | 2.21 | 1.55 | 1.59
Reversibility (%) | 24.8 | 22.8 | 22.0 | 15.4 | 15.0
Absolute reversibility (mL) | 556 | 488 | 477 | 215 | 218
Post-bronchodilator FEV1/FVC (%) | 74 | 72 | 72 | 60 | 59

The primary efficacy endpoint in Trial 1 was change from pre-treatment baseline in peak FEV1, 0-3hr at week 12. The co-primary efficacy endpoints in Trials 2 and 3 were change from pre-treatment baseline in peak FEV1, 0-3hr and change from pre-treatment baseline in trough FEV1 at week 24. Additional efficacy measures included asthma exacerbation, Asthma Control Questionnaire (ACQ), and Asthma Quality of Life Questionnaire (AQLQ).

For Trials 1, 2, and 3, SPIRIVA RESPIMAT 2.5 mcg showed statistically significant improvements in lung function over placebo when used in addition to background treatment of ICS (Table 7).

Table 7 Differences from Placebo in Peak FEV1, 0-3 hr and Trough FEV1, Adult Confirmatory Studies at Primary Endpoint Time Evaluation
Treatment (Duration) ICS Background Treatment b,c | Treatment in mcg/day | n | Peak FEV1, 0-3hr, in L a |  |  | Trough FEV1, in L a
Treatment (Duration) ICS Background Treatment b,c | Treatment in mcg/day | n | Δ from baseline | Difference from placebo |  | Δ from baseline | Difference from placebo
Treatment (Duration) ICS Background Treatment b,c | Treatment in mcg/day | n | Δ from baseline | Mean | 95% CI | Δ from baseline | Mean | 95% CI
Adult patients, age 18 years and older
Trial 1 (12 weeks) Low dose ICS | SPIRIVA RESPIMAT 2.5 mcg Placebo | 154 155 | 0.29 0.13 | 0.16 | 0.09, 0.23 | 0.13 0.02 | 0.11 | 0.04, 0.18
Trial 2 (24 weeks) Medium dose ICS | SPIRIVA RESPIMAT 2.5 mcg Salmeterol 100 mcg Placebo | 259 271 265 | 0.29 0.27 0.05 | 0.24 0.21 | 0.18, 0.29 0.16, 0.27 | 0.15 0.09 −0.03 | 0.19 0.12 | 0.13, 0.24 0.06, 0.18
Trial 3 (24 weeks) Medium dose ICS | SPIRIVA RESPIMAT 2.5 mcg Salmeterol 100 mcg Placebo | 256 264 253 | 0.29 0.25 0.08 | 0.21 0.18 | 0.16, 0.26 0.12, 0.23 | 0.16 0.09 −0.01 | 0.18 0.11 | 0.12, 0.23 0.05, 0.16
a Means adjusted for treatment, center/country, visit, visit*treatment, baseline, baseline*visit.
b Additional asthma medications allowed in stable doses prior to and throughout the trials.
c Low dose ICS = 200–400 mcg budesonide-equivalent. Medium dose ICS = 400–800 mcg budesonide-equivalent.

Trials 1, 2, and 3 also included a SPIRIVA RESPIMAT 5 mcg once daily treatment arm. In these asthma trials, the FEV1 response (change from baseline for tiotropium compared to placebo) was generally lower for the 5 mcg dose compared to the 2.5 mcg dose. The peak FEV1 0-3hr response was 16% to 20% lower for the 5 mcg dose compared to the 2.5 mcg dose in all three trials, and, the trough FEV1 response was 11% higher for the 5 mcg dose compared to the 2.5 mcg dose for one trial (Trial 1) and 18% and 24% lower for the 5 mcg dose compared to the 2.5 mcg dose for the other two trials (Trials 2 and 3).

Improvements in morning and evening peak expiratory flow (PEF) were consistent with the observed FEV1 treatment response. Examination of age, gender, smoking history, and serum IgE level subgroups did not identify differences in response among these subgroups.

The improvement of lung function compared to placebo was maintained for 24 hours (Figure 2). The bronchodilator effects of SPIRIVA RESPIMAT 2.5 mcg were apparent after first dose; however, maximum bronchodilator effect took up to 4 to 8 weeks to be achieved.

Figure 2 FEV1 Response over 24-Hours following 24-Weeks of Treatment, Trial 3

Asthma exacerbation was assessed in Trials 2 and 3 over the 24-week treatment periods. An asthma exacerbation was defined as an episode of progressive increase in ≥1 asthma symptom(s), such as shortness of breath, cough, wheezing, chest tightness or some combination of these symptoms or a decrease of a patient's best morning PEF of 30% from a patient's mean morning PEF for ≥2 consecutive days that required the initiation or increase in treatment with systemic steroids for ≥3 days. Results of asthma exacerbation are shown in Table 8.

Table 8 Exacerbations in Patients on ICS over 24-Weeks
 | Trial 2 |  | Trial 3
 | SPIRIVA RESPIMAT 2.5 mcg (N=259) | Placebo (N=265) | SPIRIVA RESPIMAT 2.5 mcg (N=256) | Placebo (N=253)
Number of patients with at least 1 event, n (%) | 9 (3.5) | 24 (9.1) | 13 (5.1) | 19 (7.5)
Rate of exacerbations per patient year
Mean rate of events | 0.08 | 0.24 | 0.13 | 0.18
Comparison to Placebo, Rate ratio (95% CI) | 0.32 (0.20, 0.51) |  | 0.70 (0.46, 1.08)
Time to first asthma exacerbation
Comparison to Placebo, Hazard ratio (95% CI) | 0.37 (0.17, 0.80) |  | 0.66 (0.33, 1.34)

Trials 2 and 3 also evaluated the rate of exacerbations and time to first asthma exacerbation for the SPIRIVA RESPIMAT 5 mcg dose. The rate of asthma exacerbations compared to placebo for SPIRIVA RESPIMAT 5 mcg was 0.78 (95% CI 0.55, 1.10) in Trial 2 and 0.76 (0.50, 1.16) in Trial 3. The hazard ratio for time to first asthma exacerbation for SPIRIVA RESPIMAT 5 mcg compared to placebo was 0.72 (95% CI 0.39, 1.35), in Trial 2 and 0.72 (0.36, 1.43) in Trial 3.

ACQ and AQLQ were assessed in Trials 2 and 3 at week 24. In Trial 2, the ACQ-7 (7 items) responder rate (defined as a change in score ≥0.5) for the SPIRIVA RESPIMAT 2.5 mcg treatment arm was 63% compared to 53% for placebo with an odds ratio of 1.47 (95% CI 1.02, 2.11). The ACQ-5 (derived from ACQ 7 by removing the FEV1 component and rescue bronchodilator component) results also had a similar trend. In Trial 2, the AQLQ responder rate (defined as a change in score ≥0.5) for the SPIRIVA RESPIMAT 2.5 mcg treatment arm was 58% compared to 50% for placebo with an odds ratio of 1.34 (95% CI 0.94, 1.93).

12-week and 48-week Parallel-Arm Design Trials in Adolescents 12-17 Years of Age

Efficacy in adolescents was based on partial extrapolation of efficacy in adults and two randomized, double-blind, placebo-controlled trials of 12 and 48 weeks duration in a total of 789 asthma patients 12 to 17 years of age (252 receiving SPIRIVA RESPIMAT 2.5 mcg once-daily, 264 receiving 5 mcg once-daily, and 273 receiving placebo). The 12-week trial enrolled patients with severe asthma who were on background treatment of ICS plus one or more controller medications (e.g. LABA). The 48-week trial enrolled patients with moderate asthma on background treatment of at least ICS. The majority of the patients in the trials were male (63.4%), Caucasian (93.7%) and had never smoked (99.9%) with a mean age of 14.3 years.

The primary efficacy endpoint in both trials was change from pre-treatment baseline in peak FEV1, 0-3hr. The primary endpoint evaluation for FEV1 was defined at week 24 for the 48-week trial and at end of the treatment period (week 12) for the 12-week trial. Given the demonstration of efficacy in the adult population, the results of the 2 trials support the efficacy of SPIRIVA RESPIMAT 2.5 mcg once daily in adolescent patients 12-17 years of age with asthma (mean difference in peak FEV1, 0-3hr from placebo for SPIRIVA RESPIMAT 2.5 mcg were 0.13 L (95% CI 0.03, 0.23) and 0.11 L (0.002, 0.22) for the 48-week and 12-week trials, respectively).

12-week and 48-week Parallel-Arm Design Trials in Pediatric Patients 6-11 Years of Age

Efficacy in pediatric patients 6-11 years of age was based on partial extrapolation of efficacy in adults and two randomized, double-blind, placebo-controlled trials of 12 and 48 weeks duration in a total of 801 asthma patients 6 to 11 years of age (271 receiving SPIRIVA RESPIMAT 2.5 mcg once-daily, 265 receiving 5 mcg once-daily, and 265 receiving placebo). The 12-week trial enrolled patients with severe asthma who were on background treatment of ICS plus one or more controller medications (e.g. LABA). The 48-week trial enrolled patients with moderate asthma on background treatment of at least ICS. The primary efficacy endpoint in both trials was change from pre-treatment baseline in peak FEV1, 0-3hr with the evaluation defined at week 24 for the 48-week trial and at end of the treatment period (week 12) for the 12-week trial. The majority of the patients in the trials were male (67.8%) and Caucasian (87.0%) with a mean age of 9.0 years.

Compared to placebo, SPIRIVA RESPIMAT 2.5 mcg once daily had a significant effect on the primary endpoint in the 48 week, but not the 12 week trial, with mean differences in peak FEV1, 0-3hr from placebo of 0.17 L (95% CI 0.11, 0.23) and 0.04 L (95% CI -0.03, 0.10) for the 48-week and 12-week trials, respectively. Given the demonstration of efficacy in the adult and adolescent population, the results support the efficacy of SPIRIVA RESPIMAT 2.5 mcg once daily in pediatric patients 6-11 years of age with asthma.

16 HOW SUPPLIED/STORAGE AND HANDLING

SPIRIVA RESPIMAT Inhalation Spray is supplied in a carton containing one SPIRIVA RESPIMAT cartridge and one SPIRIVA RESPIMAT inhaler.

The SPIRIVA RESPIMAT cartridge is provided as an aluminum cylinder with a tamper protection seal on the cap. The SPIRIVA RESPIMAT cartridge is only intended for use with the SPIRIVA RESPIMAT inhaler and should not be interchanged with any other RESPIMAT device delivered product.

The SPIRIVA RESPIMAT inhaler is a cylindrical shaped plastic inhalation device with a gray colored body and a clear base. The clear base is removed to insert the cartridge. The inhaler contains a dose indicator. The written information on the label of the gray inhaler body indicates that it is labeled for use with the SPIRIVA RESPIMAT cartridge.

SPIRIVA RESPIMAT Inhalation Spray is available in two dosage strengths, identified by dose delivered per actuation and by the color of the cap and associated container label: aqua represents 2.5 mcg per actuation; blue represents 1.25 mcg per actuation.

To deliver the recommended dosage for COPD:

- SPIRIVA RESPIMAT Inhalation Spray | 2.5 mcg/actuation | 60 metered actuations | (NDC 0597-0100-61)
- SPIRIVA RESPIMAT Inhalation Spray | 2.5 mcg/actuation | 10 metered actuations | (NDC 0597-0100-51) (institutional pack)

To deliver the recommended dosage for asthma:

- SPIRIVA RESPIMAT Inhalation Spray | 1.25 mcg/actuation | 60 metered actuations | (NDC 0597-0160-61)

The SPIRIVA RESPIMAT cartridge for each strength has a net fill weight of 4 grams and when used with the SPIRIVA RESPIMAT inhaler, is designed to deliver the labeled number of metered actuations after preparation for use. Each actuation from the SPIRIVA RESPIMAT inhaler delivers 1.25 mcg or 2.5 mcg of tiotropium (equivalent to 1.562 mcg or 3.124 mcg, respectively, of tiotropium bromide monohydrate) from the mouthpiece.

When the labeled number of actuations has been dispensed from the inhaler, the RESPIMAT locking mechanism will be engaged and no more actuations can be dispensed.

After assembly, the SPIRIVA RESPIMAT inhaler should be discarded at the latest 3 months after first use or when the locking mechanism is engaged, whichever comes first.

Keep out of reach of children. Do not spray into eyes.

Storage

Store at 20°C to 25°C (68°F to 77°F); excursions permitted to 15°C to 30°C (59°F to 86°F) [see USP Controlled Room Temperature]. Avoid freezing.

17 PATIENT COUNSELING INFORMATION

Advise the patient to read the FDA-approved patient labeling (Instructions for Use).

Not for Acute Use

Instruct patients that SPIRIVA RESPIMAT is a once-daily maintenance bronchodilator and should not be used for immediate relief of breathing problems, (i.e., as a rescue medication).

Immediate Hypersensitivity Reactions

Inform patients that anaphylaxis, angioedema (including swelling of the lips, tongue, or throat), urticaria, rash, bronchospasm, or itching, may occur after administration of SPIRIVA RESPIMAT. Advise patient to immediately discontinue treatment and consult a physician should any of these signs or symptoms develop.

Paradoxical Bronchospasm

Inform patients that SPIRIVA RESPIMAT can produce paradoxical bronchospasm. Advise patients that if paradoxical bronchospasm occurs, patients should discontinue SPIRIVA RESPIMAT.

Worsening of Narrow-Angle Glaucoma

Instruct patients to be alert for signs and symptoms of narrow-angle glaucoma (e.g., eye pain or discomfort, blurred vision, visual halos or colored images in association with red eyes from conjunctival congestion and corneal edema). Instruct patients to consult a physician immediately should any of these signs and symptoms develop.

Inform patients that care must be taken not to allow the aerosol cloud to enter into the eyes as this may cause blurring of vision and pupil dilation.

Since dizziness and blurred vision may occur with the use of SPIRIVA RESPIMAT, caution patients about engaging in activities such as driving a vehicle or operating appliances or machinery.

Worsening of Urinary Retention

Instruct patients to be alert for signs and symptoms of urinary retention (e.g., difficulty passing urine, painful urination). Instruct patients to consult a physician immediately should any of these signs or symptoms develop.

Treatment of Asthma

Instruct asthma patients that the maximum benefits may only be apparent after 4 to 8 weeks of SPIRIVA RESPIMAT treatment.

Instructions for Administering SPIRIVA RESPIMAT

It is important for patients to understand how to correctly administer SPIRIVA inhalation spray using the SPIRIVA RESPIMAT inhaler. Instruct patients that SPIRIVA inhalation spray should only be administered via the SPIRIVA RESPIMAT inhaler and the SPIRIVA RESPIMAT inhaler should not be used for administering other medications.

Instruct patients that priming SPIRIVA RESPIMAT is essential to ensure appropriate content of the medication in each actuation.

When using the unit for the first time, the SPIRIVA RESPIMAT cartridge is inserted into the SPIRIVA RESPIMAT inhaler and the unit is primed. SPIRIVA RESPIMAT patients are to actuate the inhaler toward the ground until an aerosol cloud is visible and then to repeat the process three more times. The unit is then considered primed and ready for use. If not used for more than 3 days, patients are to actuate the inhaler once to prepare the inhaler for use. If not used for more than 21 days, patients are to actuate the inhaler until an aerosol cloud is visible and then repeat the process three more times to prepare the inhaler for use.

Instruct caregivers of children that SPIRIVA RESPIMAT should be used with an adult's assistance.

Distributed by:
Boehringer Ingelheim Pharmaceuticals, Inc.
Ridgefield, CT 06877 USA

Licensed from:
Boehringer Ingelheim International GmbH

Address medical inquiries to: 1-800-542-6257.

SPIRIVA®, HANDIHALER®, and RESPIMAT® are registered trademarks of and are used under license from Boehringer Ingelheim International GmbH

Copyright © 2025 Boehringer Ingelheim International GmbH
ALL RIGHTS RESERVED

COL10534BA022025
SPL10536D

Instructions for Use

SPIRIVA® RESPIMAT® (speh REE vah - RES peh mat)
(tiotropium bromide inhalation spray), for oral inhalation use

For oral inhalation only
Do not spray SPIRIVA RESPIMAT into your eyes.

Read this Instructions for Use before you start using SPIRIVA RESPIMAT and each time you get a refill. There may be new information. This leaflet does not take the place of talking to your doctor about your medical condition or your treatment.

You will need to use this inhaler 1 time each day, at the same time each day. Each time you use it take 2 puffs.

Use SPIRIVA RESPIMAT exactly as prescribed by your doctor. Do not change your dose or how often you use SPIRIVA RESPIMAT without talking with your doctor. Children should use SPIRIVA RESPIMAT with the help of an adult, as instructed by their doctor.

Tell your doctor about all of the medicines you take, including prescription and over-the-counter medicines, vitamins, and herbal supplements. SPIRIVA RESPIMAT may affect the way some medicines work and some other medicines may affect the way SPIRIVA RESPIMAT works. Do not use other inhaled medicines with SPIRIVA RESPIMAT without talking to your doctor.

The SPIRIVA RESPIMAT inhaler has a slow-moving mist that helps you inhale the medicine.

Do not turn the clear base before inserting the cartridge.

Your SPIRIVA RESPIMAT may have either an aqua or a blue cap, depending on the strength prescribed by your doctor. The steps shown below should be followed.

How to store your SPIRIVA RESPIMAT inhaler

- Store SPIRIVA RESPIMAT at room temperature between 68°F to 77°F (20°C to 25°C).
- Do not freeze your SPIRIVA RESPIMAT cartridge and inhaler.
- If SPIRIVA RESPIMAT has not been used for more than 3 days, release 1 puff towards the ground.
- If SPIRIVA RESPIMAT has not been used for more than 21 days, repeat steps 4 to 6 under the "Prepare for first use" until a mist is visible. Then repeat steps 4 to 6 three more times.
- Keep your SPIRIVA RESPIMAT cartridge, inhaler, and all medicines out of the reach of children.

How to care for your SPIRIVA RESPIMAT inhaler
Clean the mouthpiece, including the metal part inside the mouthpiece, with a damp cloth or tissue only, at least 1 time each week. Any minor discoloration in the mouthpiece does not affect your SPIRIVA RESPIMAT inhaler.

When to get a new SPIRIVA RESPIMAT inhaler

- The scale on your inhaler shows the number of puffs in the inhaler. You should use 2 puffs 1 time each day.
- The dose indicator shows approximately how many puffs are left in the inhaler.
- When the dose indicator enters the red area of the scale you need to refill your prescription as soon as possible.
- When the dose indicator reaches the end of the red scale, your SPIRIVA RESPIMAT is empty and automatically locks. At this point, the clear base cannot be turned any further.

- Three months after insertion of cartridge, throw away the SPIRIVA RESPIMAT even if it has not been used, or when the inhaler is locked, or when it expires, whichever comes first.

Prepare for first use

1. Remove clear base
  - Keep the cap closed.
  - Press the safety catch while firmly pulling off the clear base with your other hand. Be careful not to touch the piercing element.
  - Write the discard by date on the label (3 months from the date the cartridge is inserted).

2. Insert cartridge
  - Insert the narrow end of the cartridge into the inhaler.
  - Place the inhaler on a firm surface and push down firmly until it clicks into place.

3. Replace clear base
  - Put the clear base back into place until it clicks.
  - Do not remove the clear base or the cartridge after it has been put together.

4. Turn
  - Keep the cap closed.
  - Turn the clear base in the direction of the arrows on the label until it clicks (half a turn).

5. Open
  - Open the cap until it snaps fully open.

6. Press
  - Point the inhaler toward the ground.
  - Press the dose-release button.
  - Close the cap.
  - If you do not see a mist, repeat steps 4 to 6 until a mist is seen.
  - After a mist is seen, repeat steps 4 to 6 three more times.
  - After complete preparation of your inhaler, it will be ready to deliver the number of puffs on the label.

Daily use (T O P)

Turn

- Keep the cap closed.
- Turn the clear base in the direction of the arrows on the label until it clicks (half a turn).

Open

- Open the cap until it snaps fully open.

Press

- Breathe out slowly and fully.
- Close your lips around the mouthpiece without covering the air vents.
- Point the inhaler to the back of your throat.
- While taking a slow, deep breath through your mouth, Press the dose-release button and continue to breathe in.
- Hold your breath for 10 seconds or for as long as comfortable.
- Repeat Turn, Open, Press (TOP) for a total of 2 puffs.
- Close the cap until you use your inhaler again.

Answers to Common Questions

It is difficult to insert the cartridge deep enough:

Did you accidentally turn the clear base before inserting the cartridge? Open the cap, press the dose-release button, then insert the cartridge.

Did you insert the cartridge with the wide end first? Insert the cartridge with the narrow end first.

I cannot press the dose-release button:

Did you turn the clear base? If not, turn the clear base in a continuous movement until it clicks (half a turn).

Is the dose indicator on the SPIRIVA RESPIMAT pointing to 0 (zero)? The SPIRIVA RESPIMAT inhaler is locked after the labeled number of puffs have been used. Prepare and use your new SPIRIVA RESPIMAT inhaler.

I cannot turn the clear base:

Did you turn the clear base already? If the clear base has already been turned, follow steps "Open" and "Press" under "Daily use" to get your medicine.

Is the dose indicator on the SPIRIVA RESPIMAT pointing to 0 (zero)? The SPIRIVA RESPIMAT inhaler is locked after the labeled number of puffs have been used. Prepare and use your new SPIRIVA RESPIMAT inhaler.

The dose indicator on the SPIRIVA RESPIMAT reaches 0 (zero) too soon:

Did you use SPIRIVA RESPIMAT as indicated (2 puffs 1 time each day)?

Did you turn the clear base before you inserted the cartridge? The dose indicator counts each turn of the clear base regardless whether a cartridge has been inserted or not.

Did you spray in the air often to check whether the SPIRIVA RESPIMAT is working? After you have prepared SPIRIVA RESPIMAT, no test-spraying is required if used daily.

Did you insert the cartridge into a used SPIRIVA RESPIMAT? Always insert a new cartridge into a new SPIRIVA RESPIMAT.

My SPIRIVA RESPIMAT sprays automatically:

Was the cap open when you turned the clear base? Close the cap, then turn the clear base.

Did you press the dose-release button when turning the clear base? Close the cap, so the dose-release button is covered, then turn the clear base.

Did you stop when turning the clear base before it clicked? Turn the clear base in a continuous movement until it clicks (half a turn).

My SPIRIVA RESPIMAT does not spray:

Did you insert a cartridge? If not, insert a cartridge.

Did you repeat Turn, Open, Press (TOP) less than 3 times after inserting the cartridge? Repeat Turn, Open, Press (TOP) 3 times after inserting the cartridge as shown in steps 4 to 6 under "Prepare for first use".

Is the dose indicator on the SPIRIVA RESPIMAT pointing to 0 (zero)? You have used up all your medicine and the inhaler is locked.

For more information about SPIRIVA RESPIMAT, including current prescribing information, a video demonstration or a Quick Start Guide on how to use SPIRIVA RESPIMAT, go to www.spiriva.com, scan the code, or call 1-800-542-6257.

This Instructions for Use has been approved by the U.S. Food and Drug Administration.

Distributed by: Boehringer Ingelheim Pharmaceuticals, Inc., Ridgefield, CT 06877 USA

Licensed from:
Boehringer Ingelheim International GmbH

SPIRIVA® and RESPIMAT® are registered trademarks of and are used under license from Boehringer Ingelheim International GmbH

Copyright © 2025 Boehringer Ingelheim International GmbH
ALL RIGHTS RESERVED

Revised: January 2025

COL10534BA022025
SPL10536D

PRINCIPAL DISPLAY PANEL - 1.25 mcg Cartridge Carton

NDC 0597-0160-61

Spiriva® Respimat®
(tiotropium bromide inhalation spray)

1.25 mcg/actuation*

FOR ORAL INHALATION ONLY

ATTENTION PHARMACIST:
Dispense with Instructions for Use

Rx only

4 Grams
60 Metered Inhalations
(Two inhalations equal one dose)

Boehringer
Ingelheim

PRINCIPAL DISPLAY PANEL - 2.5 mcg Cartridge Carton

NDC 0597-0100-61

Spiriva® Respimat®
(tiotropium bromide inhalation spray)

2.5 mcg/actuation*

FOR ORAL INHALATION ONLY

ATTENTION PHARMACIST:
Dispense with Instructions for Use

Rx only

4 Grams
60 Metered Inhalations
(Two inhalations equal one dose)

Boehringer
Ingelheim